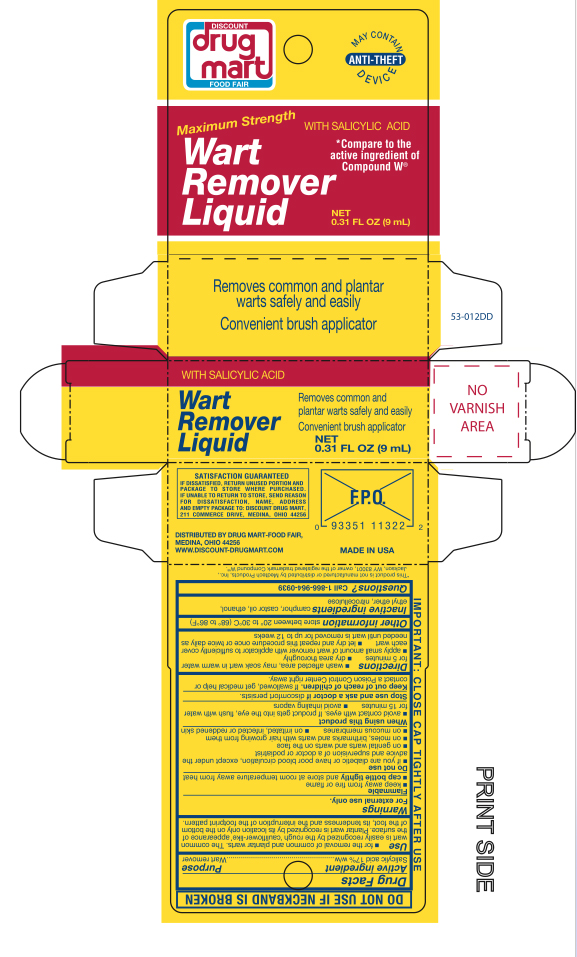 DRUG LABEL: Salicylic Acid
NDC: 53943-009 | Form: LIQUID
Manufacturer: Discount Drug Mart
Category: otc | Type: HUMAN OTC DRUG LABEL
Date: 20251007

ACTIVE INGREDIENTS: SALICYLIC ACID 0.17 mg/9 mL
INACTIVE INGREDIENTS: PYROXYLIN; CAMPHOR (NATURAL); CASTOR OIL

Discount Drug Mart Wart Remover Liquid

Active ingredient

Salicylic acid 17% w/w

Purpose

Wart Remover

Use

For the removal of common and plantar warts. The common wart has a rough 'cauliflower-like' appearance of the surface. The plantar wart exists only on the bottom of the foot and interrupts footprint pattern.

Warnings

For external use only.

Flammable

- keep away from fire or flame
- cap bottle tightly and store at room temperature away heat

Do not use

- if you are a diabetic or have poor blood circulation, except under the advice and supervision of a doctor or podiatrist
- on irritated, infected amd reddened skin
- on genital warts and warts on the face
- on moles, birthmarks and warts with hair growing from them
- on mucous membranes

When using this product

- avoid contact with eyes. If product gets into the eyes, flush with water for 15 minutes
- avoid inhaling vapors

Stop use and ask doctor

if discomfort persists

Keep out of reach of children.

If swallowed, get medical help or contact a Poison Control Center right away.

Directions

- wash affected area, may soak wart in warm water for 5 minutes
- dry thoroughly
- apply small amount of wart remover with applicator to sufficiently cover each wart
- let dry and repeat this procedure once or twice daily, until wart is completed removed, for up to 12 weeks

Other information

store between 20o to 30oC (68o to 86oF)

Inactive ingredient

camphor, castro oil, ethanol, ethyl ether, nitrocellulose

Questions?

Call 1-866-964-0939

Principal Display Panel

Discount Drug Mart

Maximum Strength

Wart Remover Liquid

with Salicylic Acid

Removes common and plantar warts safely and easily

Convenient brush applicator

NET 0.31 FL OZ (9 mL)